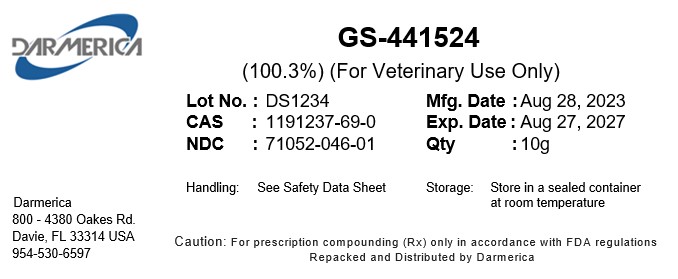 DRUG LABEL: GS-441524
NDC: 71052-046 | Form: POWDER
Manufacturer: DARMERICA, LLC
Category: other | Type: BULK INGREDIENT - ANIMAL DRUG
Date: 20250827

ACTIVE INGREDIENTS: GS-441524 1 g/1 g

GS-441524